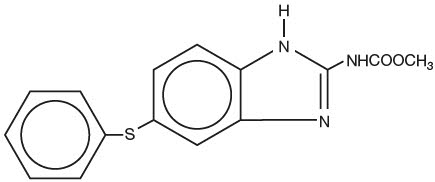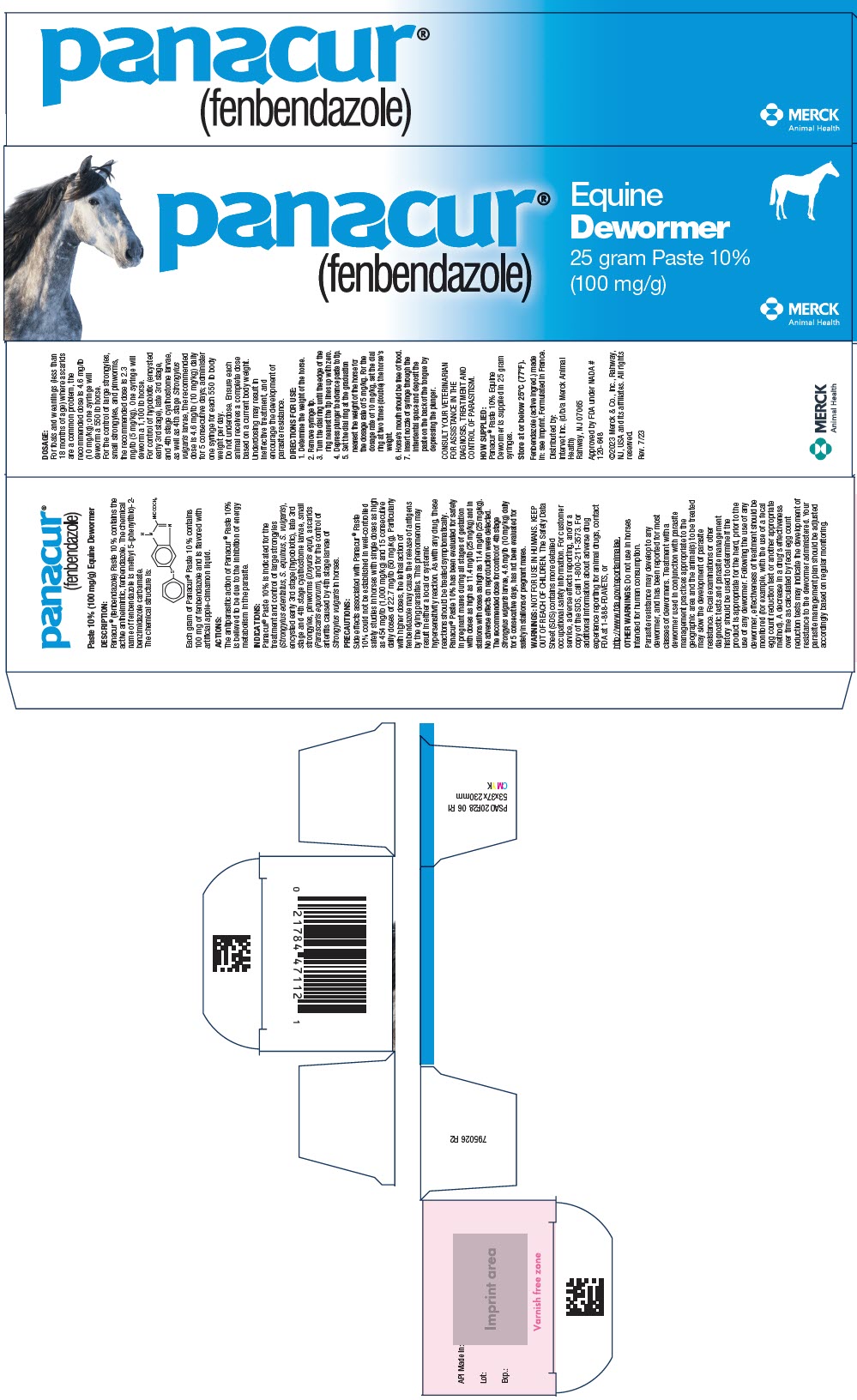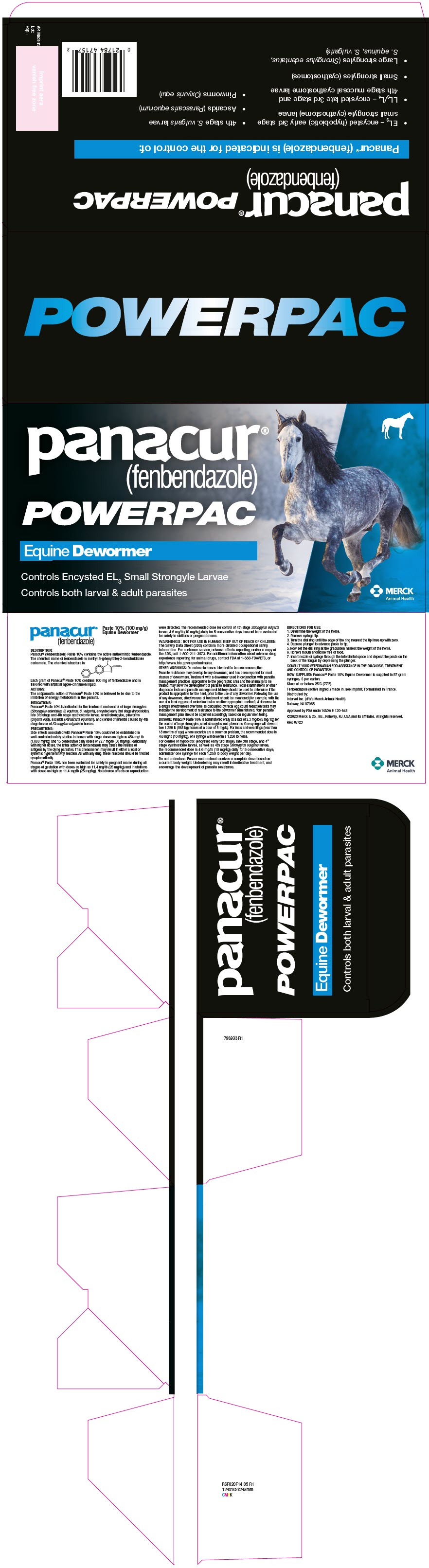 DRUG LABEL: Panacur
NDC: 57926-081 | Form: PASTE
Manufacturer: Merck Sharp & Dohme Corp.
Category: animal | Type: OTC ANIMAL DRUG LABEL
Date: 20250820

ACTIVE INGREDIENTS: FENBENDAZOLE 100 mg/1 g

panacur®
(fenbendazole)

Paste 10% (100 mg/g) Equine Dewormer

DESCRIPTION:

Panacur® (fenbendazole) Paste 10% contains the active anthelmintic, fenbendazole. The chemical name of fenbendazole is methyl 5-(phenylthio)-2-benzimidazole carbamate.

The chemical structure is:

Each gram of Panacur® Paste 10% contains 100 mg of fenbendazole and is flavored with artificial apple-cinnamon liquid.

ACTIONS:

The antiparasitic action of Panacur® Paste 10% is believed to be due to the inhibition of energy metabolism in the parasite.

INDICATIONS:

Panacur® Paste 10% is indicated for the treatment and control of large strongyles (Strongylus edentatus, S. equinus, S. vulgaris), encysted early 3rd stage (hypobiotic), late 3rd stage and 4th stage cyathostome larvae, small strongyles, pinworms (Oxyuris equi), ascarids (Parascaris equorum), and for the control of arteritis caused by 4th stage larvae of Strongylus vulgaris in horses.

PRECAUTIONS:

Side effects associated with Panacur® Paste 10% could not be established in well-controlled safety studies in horses with single doses as high as 454 mg/lb (1,000 mg/kg) and 15 consecutive daily doses of 22.7 mg/lb (50 mg/kg). Particularly with higher doses, the lethal action of fenbendazole may cause the release of antigens by the dying parasites. This phenomenon may result in either a local or systemic hypersensitivity reaction. As with any drug, these reactions should be treated symptomatically. Panacur® Paste 10% has been evaluated for safety in pregnant mares during all stages of gestation with doses as high as 11.4 mg/lb (25 mg/kg) and in stallions with doses as high as 11.4 mg/lb (25 mg/kg). No adverse effects on reproduction were detected. The recommended dose for control of 4th stage Strongylus vulgaris larvae, 4.6 mg/lb (10 mg/kg) daily for 5 consecutive days, has not been evaluated for safety in stallions or pregnant mares.

WARNINGS:

NOT FOR USE IN HUMANS. KEEP OUT OF REACH OF CHILDREN. The Safety Data Sheet (SDS) contains more detailed occupational safety information. For customer service, adverse effects reporting, and/or a copy of the SDS, call 1-800-211-3573. For additional information about adverse drug experience reporting for animal drugs, contact FDA at 1-888-FDAVETS, or http://www.fda.gov/reportanimalae.

FOOD SAFETY WARNING

OTHER WARNINGS: Do not use in horses intended for human consumption.

Parasite resistance may develop to any dewormer, and has been reported for most classes of dewormers. Treatment with a dewormer used in conjunction with parasite management practices appropriate to the geographic area and the animal(s) to be treated may slow the development of parasite resistance. Fecal examinations or other diagnostic tests and parasite management history should be used to determine if the product is appropriate for the herd, prior to the use of any dewormer. Following the use of any dewormer, effectiveness of treatment should be monitored (for example, with the use of a fecal egg count reduction test or another appropriate method). A decrease in a drug's effectiveness over time as calculated by fecal egg count reduction tests may indicate the development of resistance to the dewormer administered. Your parasite management plan should be adjusted accordingly based on regular monitoring.

DOSAGE:

For foals and weanlings (less than 18 months of age) where ascarids are a common problem, the recommended dose is 4.6 mg/lb (10 mg/kg); one syringe will deworm a 550 lb horse.

For the control of large strongyles, small strongyles, and pinworms, the recommended dose is 2.3 mg/lb (5 mg/kg). One syringe will deworm a 1,100 lb horse.

For control of hypobiotic (encysted early 3rd stage), late 3rd stage, and 4th stage cyathostome larvae, as well as 4th stage Strongylus vulgaris larvae, the recommended dose is 4.6 mg/lb (10 mg/kg) daily for 5 consecutive days; administer one syringe for each 550 Ib body weight per day.

Do not underdose. Ensure each animal receives a complete dose based on a current body weight. Underdosing may result in ineffective treatment, and encourage the development of parasite resistance.

DOSAGE AND ADMINISTRATION

DOSAGE: Panacur® Paste 10% is administered orally at a rate of 2.3 mg/lb (5 mg/ kg) for the control of large strongyles, small strongyles, and pinworms. One syringe will deworm two 1,250 lb (568 kg) horses at a dose of 5 mg/kg. For foals and weanlings (less than 18 months of age) where ascarids are a common problem, the recommended dose is 4.6 mg/lb (10 mg/kg); one syringe will deworm a 1,250 lb horse.

For control of hypobiotic (encysted early 3rd stage), late 3rd stage, and 4th stage cyathostome larvae, as well as 4th stage Strongylus vulgaris larvae, the recommended dose is 4.6 mg/lb (10 mg/kg) daily for 5 consecutive days; administer one syringe for each 1,250 Ib body weight per day.

Do not underdose. Ensure each animal receives a complete dose based on a current body weight. Underdosing may result in ineffective treatment, and encourage the development of parasite resistance.

DIRECTIONS FOR USE:

1. Determine the weight of the horse.
2. Remove syringe tip.
3. Turn the dial ring until the edge of the ring nearest the tip lines up with zero.
4. Depress plunger to advance paste to tip.
5. Set the dial ring at the graduation nearest the weight of the horse for the dosage rate of 5 mg/kg. For the dosage rate of 10 mg/kg, set the dial ring at two times (double) the horse's weight.
6. Horse's mouth should be free of food.
7. Insert nozzle of syringe through the interdental space and deposit the paste on the back of the tongue by depressing the plunger.

CONSULT YOUR VETERINARIAN FOR ASSISTANCE IN THE DIAGNOSIS, TREATMENT AND CONTROL OF PARASITISM.

HOW SUPPLIED:

Panacur® Paste 10% Equine Dewormer is supplied in 25 gram syringes.

STORAGE AND HANDLING

Store at or below 25°C (77°F).

HOW SUPPLIED

HOW SUPPLIED: Panacur® Paste 10% Equine Dewormer is supplied in 57 gram syringes, 5 per carton.

STORAGE AND HANDLING

Store at or below 25°C (77°F).

Fenbendazole (active ingred.) made in: see imprint. Formulated in France.

Distributed by:
Intervet Inc. (d/b/a Merck Animal Health)
Rahway, NJ 07065

Approved by FDA under NADA #120-648

©2023 Merck & Co., Inc., Rahway, NJ, USA and its affiliates. All rights reserved.

Rev. 7/23

MERCK
Animal Health

PRINCIPAL DISPLAY PANEL - 25 gram Syringe Carton

panacur®
(fenbendazole)

Equine
Dewormer

25 gram Paste 10%
(100 mg/g)

MERCK
Animal Health

PRINCIPAL DISPLAY PANEL - 57 gram Syringe Carton

panacur®
(fenbendazole)

POWERPAC

Equine Dewormer

Controls Encysted EL3 Small Strongyle Larvae

Controls both larval & adult parasites

MERCK
Animal Health